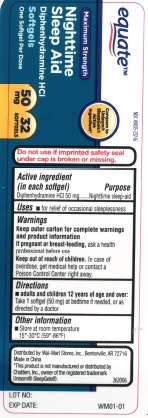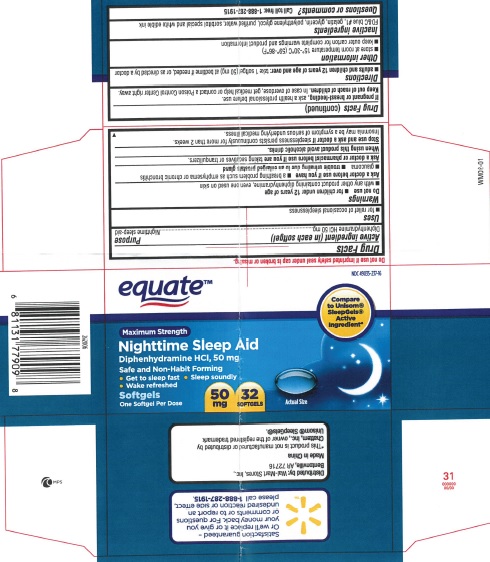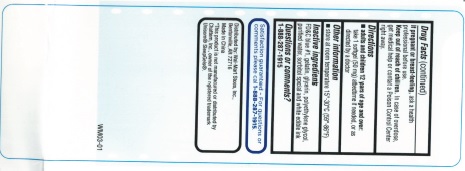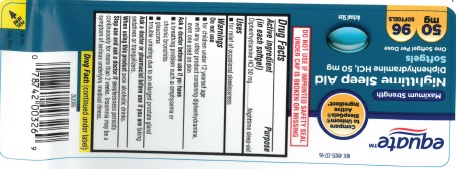 DRUG LABEL: NIGHTTIME SLEEP AID Maximum Strength
NDC: 49035-237 | Form: CAPSULE, LIQUID FILLED
Manufacturer: EQUATE (Walmart Stores, Inc.)
Category: otc | Type: HUMAN OTC DRUG LABEL
Date: 20191121

ACTIVE INGREDIENTS: DIPHENHYDRAMINE HYDROCHLORIDE 50 mg/1 1
INACTIVE INGREDIENTS: FD&C BLUE NO. 1; GELATIN; GLYCERIN; POLYETHYLENE GLYCOL, UNSPECIFIED; WATER; SORBITOL

Nighttime Sleep-Aid

Drug Facts

Active ingredient (in each softgel)

Diphenhydramine HCl 50 mg

Purpose

Nighttime sleep-aid

Uses

- for the relief of occasional sleeplessness

Warnings

Do not use

- for children under 12 years of age
- with any other product containing diphenhydramine, even one used on skin

Ask a doctor before use if you have

- a breathing problem such as emphysema or chronic bronchitis
- glaucoma
- trouble urinating due to an enlarged prostate gland

Ask a doctor or pharmacist before use if you are taking sedatives or tranquilizers

When using this product avoid alcoholic drinks

Stop use and ask a doctor if sleeplessness persists continuously for more than 2 weeks. Insomnia may be a symptom of serious underlying medical illness.

PREGNANCY OR BREAST FEEDING

If pregnant or breast-feeding, ask a health professional before use.

Keep out of reach of children. In case of overdose, get medical help or contact a Poison Control Center right away.

Directions

- adults and children 12 years of age and over: take 1 softgel (50 mg) at bedtime if needed, or as directed by adoctor

Other information

- store at 15°-30°C (59°-86°F)

Inactive ingredients

FD&C blue #1, gelatin, glycerin, polyethylene glycol, purified water, sorbitol special and white edible ink

Questions or comments?

Call toll free 1-888-287-1915

PRINCIPAL DISPLAY PANEL - 32ct Carton and Bottle Label

Nighttime Sleep-Aid Maximum Strength

Diphenhydramine HCl, 50 mg 32 Softgels

Compare to Unisom® SleepGels® Active Ingredient*

NDC 49035-237-16

Distributed by: Wal-Mart Stores, Inc. Bentonville, AR 72716

*This product is not manufactured or distributed by Chattem, Inc., owner of the registered trademark Unisom® SleepGels®

PRINCIPAL DISPLAY PANEL - 96ct Bottle Label

Nighttime Sleep-Aid Maximum Strength

Diphenhydramine HCl, 50 mg 96 Softgels

Compare to Unisom® SleepGels® Active Ingredient*

NDC 49035-237-96

Distributed by: Wal-Mart Stores, Inc. Bentonville, AR 72716

*This product is not manufactured or distributed by Chattem, Inc., owner of the registered trademark Unisom® SleepGels®